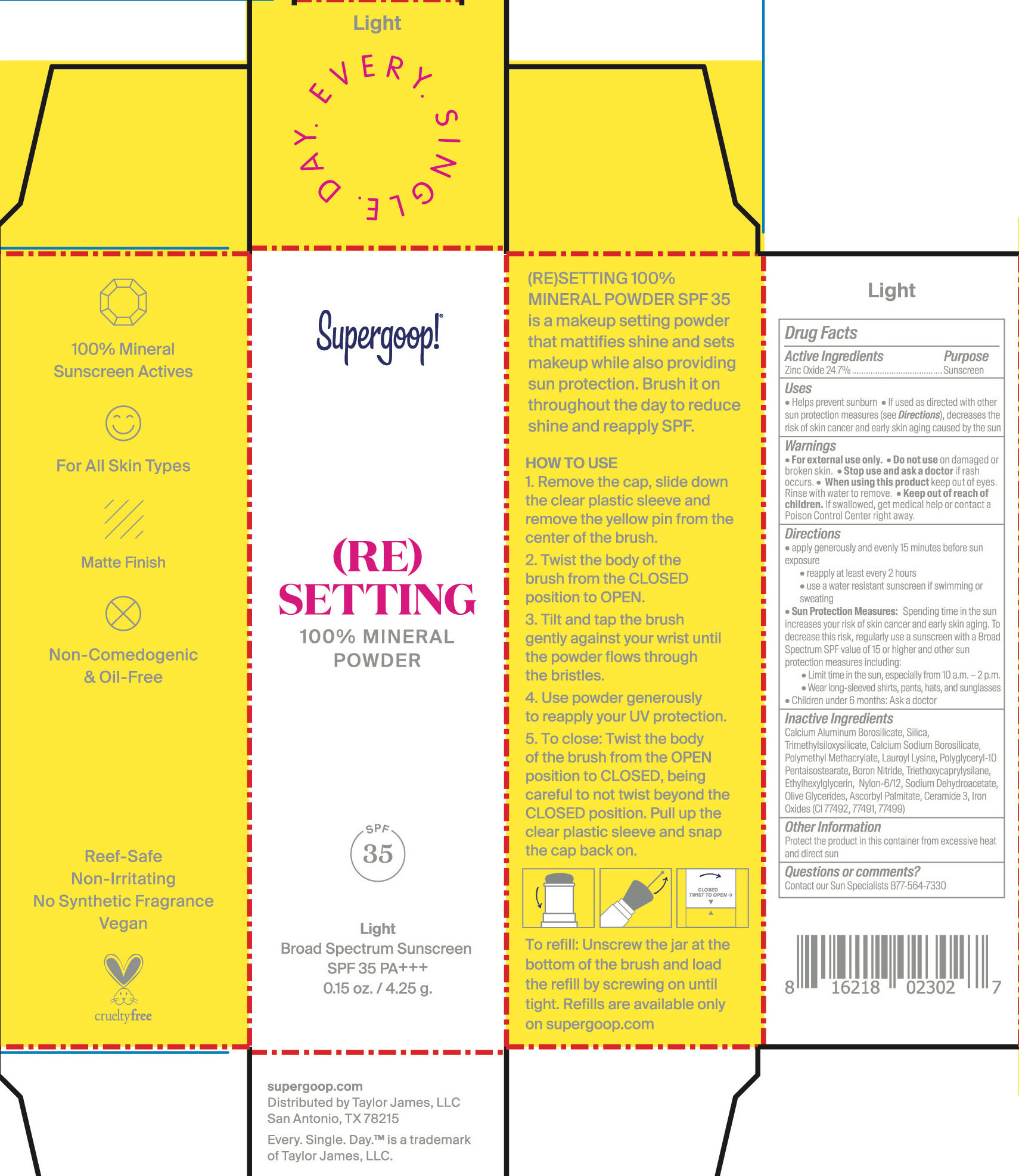 DRUG LABEL: (Re) Setting 100% mineral Powder Light Broad Spectrum SPF 35
NDC: 75936-166 | Form: POWDER
Manufacturer: Supergoop, LLC
Category: otc | Type: HUMAN OTC DRUG LABEL
Date: 20241204

ACTIVE INGREDIENTS: ZINC OXIDE 24.7 g/100 g
INACTIVE INGREDIENTS: TRIETHOXYCAPRYLYLSILANE; ASCORBYL PALMITATE; SILICON DIOXIDE; ETHYLHEXYLGLYCERIN; POLY(METHYL METHACRYLATE; 450000 MW); TRIMETHYLSILOXYSILICATE (M/Q 0.6-0.8); LAUROYL LYSINE; FERRIC OXIDE YELLOW; CALCIUM ALUMINUM BOROSILICATE; FERRIC OXIDE RED; FERROSOFERRIC OXIDE; CERAMIDE 3; BORON NITRIDE; SODIUM DEHYDROACETATE

(Re) Setting 100% mineral Powder Light Broad Spectrum SPF 35

ACTIVE INGREDIENT

Zinc Oxide 24.7% Purpose Sunscreen

PURPOSE

Sunscreen

- Helps prevent sunburn
- If used as directed with other sun protection measures (see Directions), decreases the risk of skin cancer and early skin aging caused by the sun

Keep out of reach of children. If swallowed, get medical help or contact a Poison Control Center right away.

Stop use and ask a Doctor if rash occurs.

WARNINGS

For external use only.

Do not use on damaged or broken skin.

When using this product keep out of eyes. Rinse with water to remove.

DOSAGE AND ADMINISTRATION

- apply generously and evenly 15 minutes before sun exposure
- reapply at least every 2 hours
- use a water resistant sunscreen if swimming or sweating
- Sun Protection Measures: Spending time in the sun increases your risk of skin cancer and early skin aging. To decrease this risk, regularly use a sunscreen with a Broad Spectrum SPF value of 15 or higher and other sun protection measures including:
- Limit time in the sun, especially from 10 a.m. - 2 p.m.
- Wear long-sleeved shirts, pants, hats, and sunglasses
- Children under 6 months: Ask a doctor.

INACTIVE INGREDIENT

Calcium Aluminum Borosilicate, Silica, Trimethylsiloxysilicate, Calcium Sodium Borosilicate, Polymethyl Methacrylate, Lauroyl Lysine, Polyglyceryl-10 Pentaisostearate, Boron Nitride, Triethoxycaprylysilane, Ethylhexylglycerin, Nylon-6/12, Sodium Dehydroacetate, Olive Glycerides, Ascorbyl Palmitate, Ceramide 3, Iron OXides (CI 77492, 77491, 77499)

PACKAGE LABEL

Supergoop!

(RE) SETTING

100% MINERAL POWDER

SPF 35

Light

Broad Spectrum Sunscreen

SPF 35 PA+++

0.15 oz./4.25 g